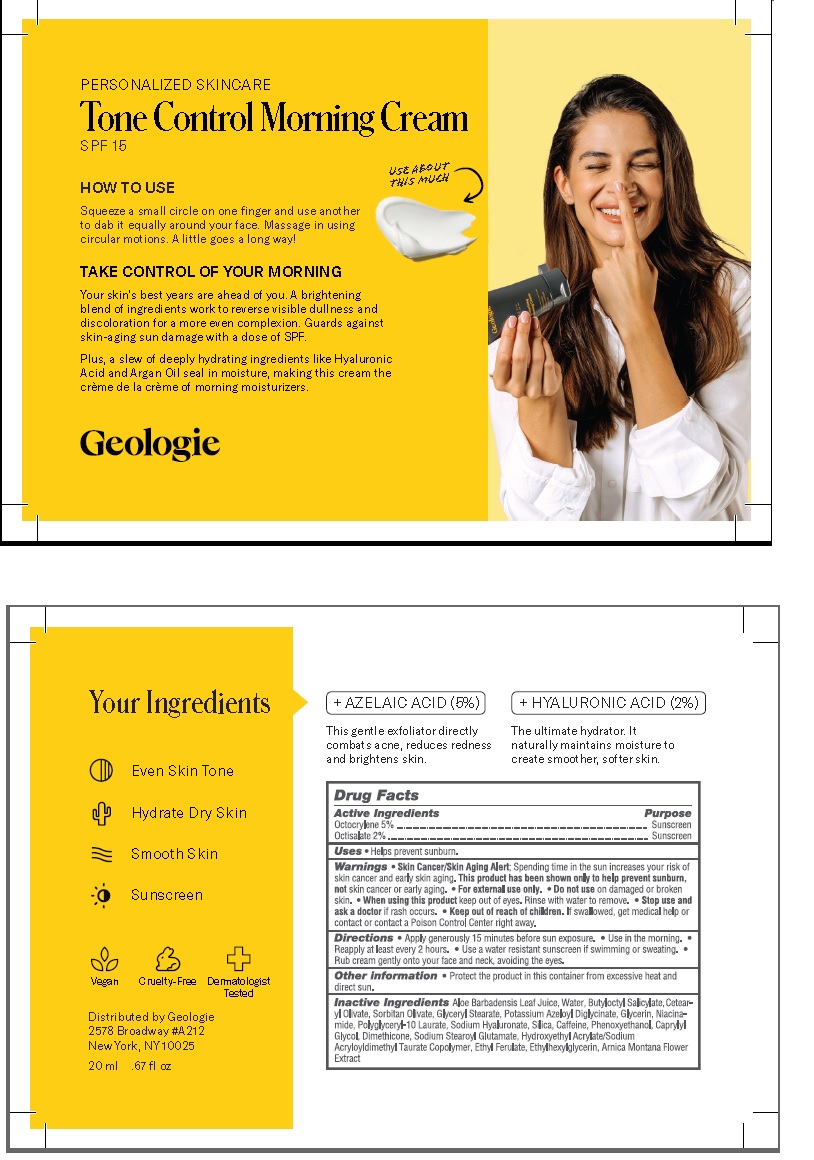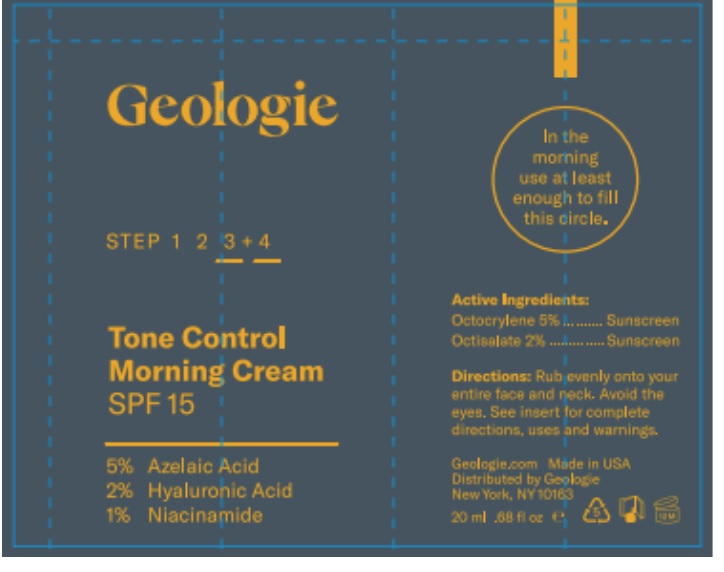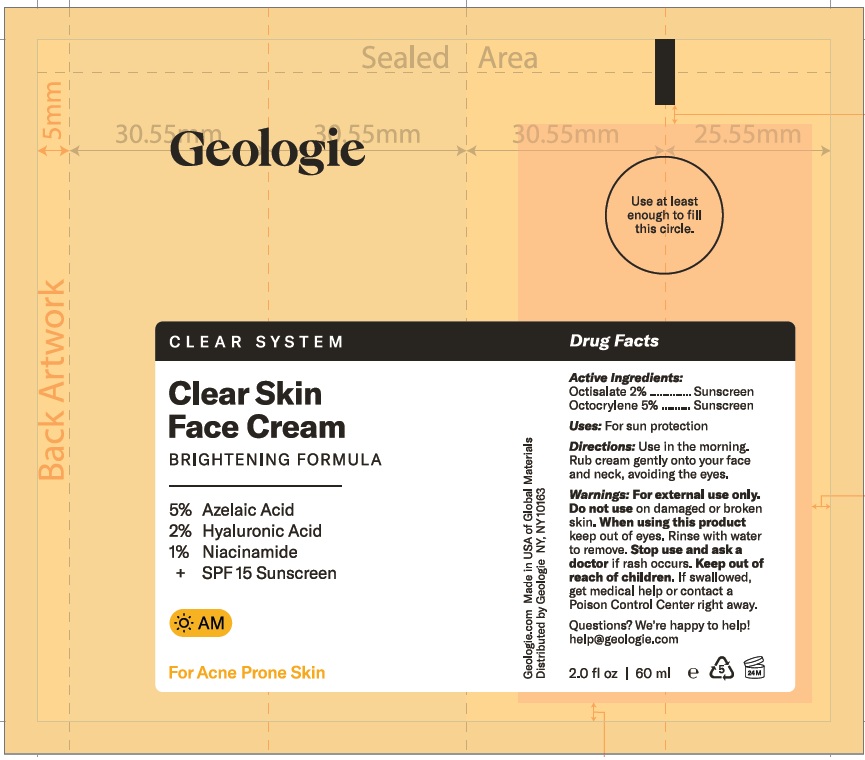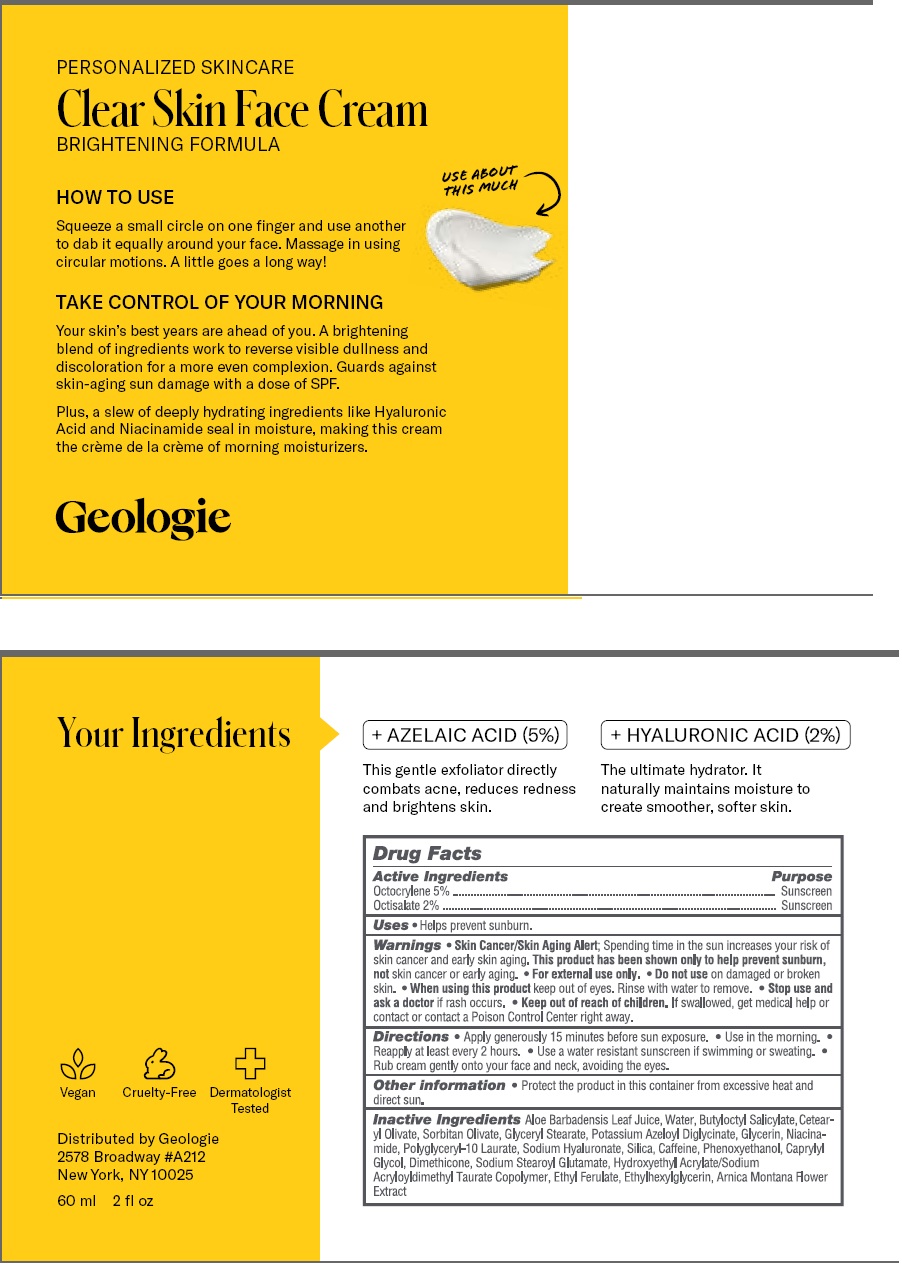 DRUG LABEL: Tone Control Morning Cream SPF 15
NDC: 54111-173 | Form: CREAM
Manufacturer: Bentley Laboratories, LLC
Category: otc | Type: HUMAN OTC DRUG LABEL
Date: 20241227

ACTIVE INGREDIENTS: OCTOCRYLENE 5.0 g/100 mL; OCTISALATE 2.0 g/100 mL
INACTIVE INGREDIENTS: ALOE VERA LEAF; WATER; BUTYLOCTYL SALICYLATE; CETEARYL OLIVATE; SORBITAN OLIVATE; GLYCERYL MONOSTEARATE; POTASSIUM AZELOYL DIGLYCINATE; GLYCERIN; NIACINAMIDE; POLYGLYCERYL-10 LAURATE; SILICON DIOXIDE; CAFFEINE; PHENOXYETHANOL; Caprylyl Glycol; DIMETHICONE; SODIUM STEAROYL GLUTAMATE; HYDROXYETHYL ACRYLATE/SODIUM ACRYLOYLDIMETHYL TAURATE COPOLYMER (100000 MPA.S AT 1.5%); ETHYL FERULATE; ETHYLHEXYLGLYCERIN; ARNICA MONTANA FLOWER

Tone Control Morning Cream SPF 15

DRUG FACTS

Active Ingredients

Octocrylene 5%

Octisalate 2%

Purpose .... Sunscreem

INDICATIONS AND USAGE

Uses: Helps prevent sunburn.

WARNINGS

Warnings •Skin Cancer/Skin Aging Alert: Spending too much time in the sun increases your risk of
skin cancer and early skin aging. This product has been shown to only help prevent sunburn,
not skin cancer or early skin aging. • For external use only. • Do not use on damaged or broken
skin. • When using this product, keep out of eyes. Rinse with water to remove. • Stop use and
ask a doctor if rash occurs.

KEEP OUT OF REACH OF CHILDREN

Keep out of the reach of children. If swallowed get medical help or contact a Poison Control center right away.

DOSAGE AND ADMINISTRATION

Directions• Apply generously 15 minutes before sun exposure. • Use in the morning.
• Reapply every 2 hours. • Use a water resistant sunscreen if swimming or sweating. • Rub
cream gently into your face and neck, avoiding the eyes.

Other information • Protect the product in this container from excessive heat and direct sun.

INACTIVE INGREDIENT

Inactive Ingredients Aloe Barbadensis Leaf Juice, Water, Butyloctyl Salicylate, Cetear-
yl Olivate, Sorbitan Olivate, Glyceryl Stearate, Potassium Azeloyl Diglycinate, Glycerin, Niacina-
mide, Polyglyceryl-10 Laurate, Sodium Hyaluronate, Silica, Caffeine, Phenoxyethanol, Caprylyl
Glycol, Dimethicone, Sodium Stearoyl Glutamate, Hydroxyethyl Acrylate/Sodium
Acryloyldimethyl Taurate Copolymer, Ethyl Ferulate, Ethylhexylglycerin, Arnica Montana Flower
Extract

Product Labeling

Tone Control Morning Cream SPF 15
SPF 15

Distributed by Geologie
2578 Broadway #A212
New York, NY 10025

20 ml .67 fl oz

20 mL Label

60 mL Label

res